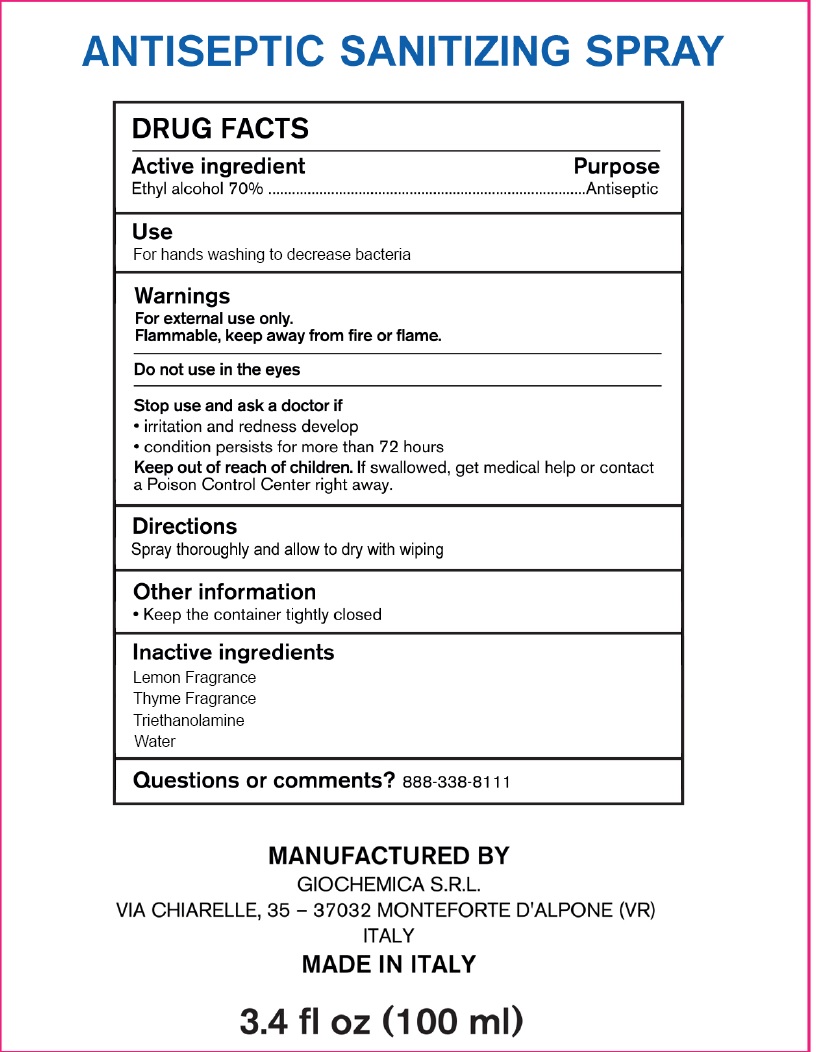 DRUG LABEL: Antiseptic Sanitizing
NDC: 80365-001 | Form: LIQUID
Manufacturer: Adam br srl
Category: otc | Type: HUMAN OTC DRUG LABEL
Date: 20210518

ACTIVE INGREDIENTS: ALCOHOL 70 mL/100 mL
INACTIVE INGREDIENTS: TROLAMINE; WATER

Antiseptic Sanitizing Spray

Active ingredient

Ethyl alcohol 70%

Purpose

Antiseptic

Use

For hands washing to decrease bacteria

Warnings

For external use only.

Flammable, keep away from fire or flame.

Do not use

in the eyes

Stop use and ask a doctor if

- irritation and redness develop
- condition persists for more than 72 hours

Keep out of reach of children.

If swallowed, get medical help or contact a Poison Control Center right away.

Dierctions

Spray thoroughly and allow to dry with wiping

Other information

- Keep the container tightly closed

Inactive ingredients

Lemon Fragrance
Thyme Fragrance
Triethanolamine
Water

Questions or comments?

888-338-8111